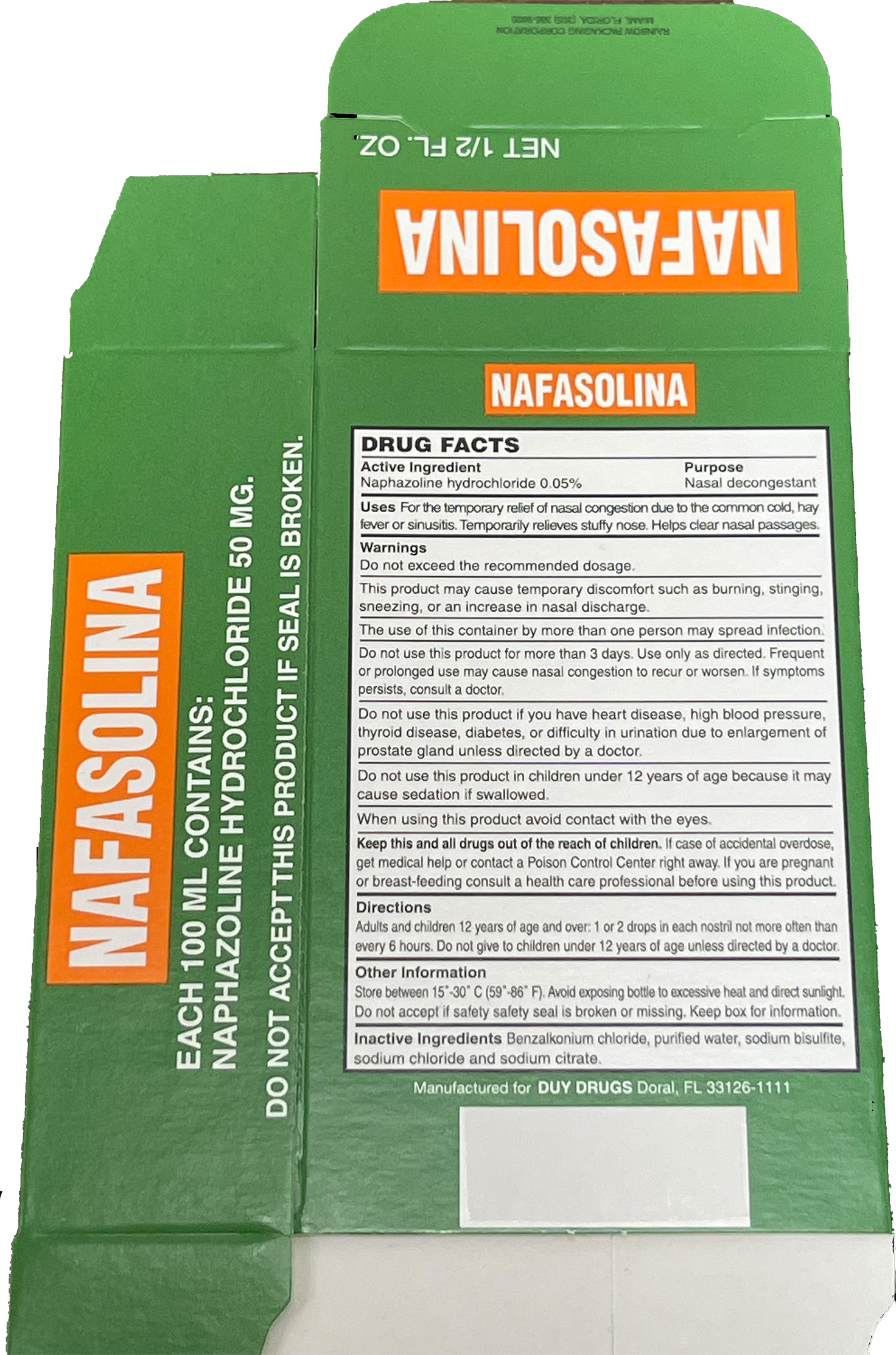 DRUG LABEL: NAFASOLINA
NDC: 12539-146 | Form: SOLUTION/ DROPS
Manufacturer: Doral Pharmamedics Inc DBA AG Marin Pharmaceuticals
Category: otc | Type: HUMAN OTC DRUG LABEL
Date: 20251218

ACTIVE INGREDIENTS: NAPHAZOLINE HYDROCHLORIDE 50 mg/100 mL
INACTIVE INGREDIENTS: WATER 95.624 mg/100 mL; SODIUM BISULFITE 1 mg/100 mL; BENZALKONIUM CHLORIDE 1 mg/100 mL; SODIUM CITRATE 1 mg/100 mL; SODIUM CHLORIDE 1 mg/100 mL

Naphazoline hydrochloride 0.05%

ACTIVE INGREDIENT

Naphazoline hydrochloride 0.05% v/v. Purpose: Nasal decongestant

Keep out of reach of children. In case of accidental overdose, get medical help or contact a Poison Control Center right away.

Stop using this product after 3 days.

If symptoms persist, stop, and consult a doctor.

INACTIVE INGREDIENT

Benzalkonium chloride, purified water, sodium bisulfite, sodium chloride, and sodium citrate.

PURPOSE

For the temporary relief of nasal congestion due to the common cold, hay fever, or sinusitis.

Temporarily relieves a stuffy nose.

Helps clear nasal passages.

WHEN USING

Use for the temporary relief of nasal congestion due to the common cold, hay fever, or sinusitis.

DOSAGE AND ADMINISTRATION

Adults and children 12 years of age and over: 1 or 2 drops in each nostril not more often than every 6 hours. Do not give to children under 12 years of age unless directed by a doctor.

WARNINGS

Do not exceed recommended dosage.

This product may cause temporary discomfort such as burning, stinging, sneezing, or an increase in nasal discharge.

The use of this container by more than one person may spread infection.

Do not use this product for more than 3 days. Use only as directed. Frequent or prolonged use may cause nasal congestion to recur or worsen. If symptoms persist, consult a doctor.

Do not use this product if you have heart disease, high blood pressure, thyroid disease, diabetes, or difficulty in urination due to enlargement of the prostate gland unless directed by a doctor.

Do not use this product in children under 12 years of age because it may cause sedation if swallowed.

When using this product avoid contact with the eyes.

DO NOT USE

If you are pregnant or breast-feeding consult a health care professional before using this product.

Do not use this product if you are now taking a prescription monoamine oxidase inhibitor (MAOI) (certain drugs for depression, psychiatric or emotional conditions, or Parkinson's disease), or for 2

weeks after stopping the MAOI drug. If you are uncertain whether your prescription drug contains an MAOI, consult a health professional before taking this product.

Do not use this product for more than 3 days. Use only as directed. Frequent or prolonged use may cause nasal congestion to recur or worsen. If symptoms persist, consult a doctor.

Do not use this product if you have heart disease, high blood pressure, thyroid disease, diabetes, or difficulty in urination due to enlargement of the prostate gland unless directed by a doctor.

Do not use this product in children under 12 years of age because it may cause sedation if swallowed.

Do not use this product in a child who has heart disease, high blood pressure, thyroid disease, or diabetes unless directed by a doctor.

This product is for nasal use only.

When using this product avoid contact with the eyes. In case of contact with eyes, rinse eyes thoroughly with water.

INDICATIONS AND USAGE

Naphazoline hydrochloride 0.05% nasal drops are indicated for the temporary relief of nasal congestion due to the common cold, hay fever, or sinusitis. Temporarily relieves a stuffy nose. Helps clear nasal passages.

PACKAGE LABEL

Principal Display Panel

0.5 FL. OZ NDC: 12539-146-02